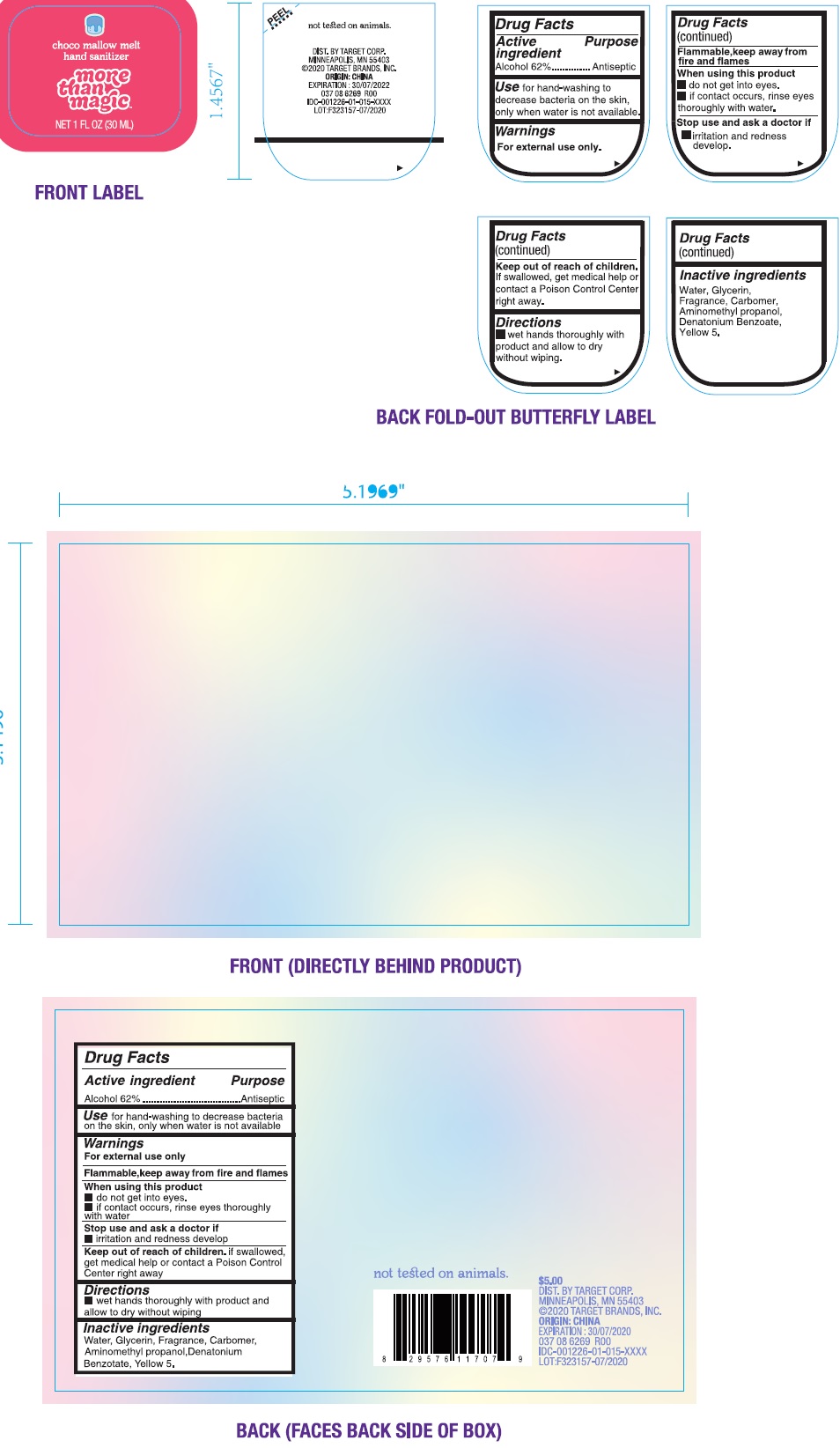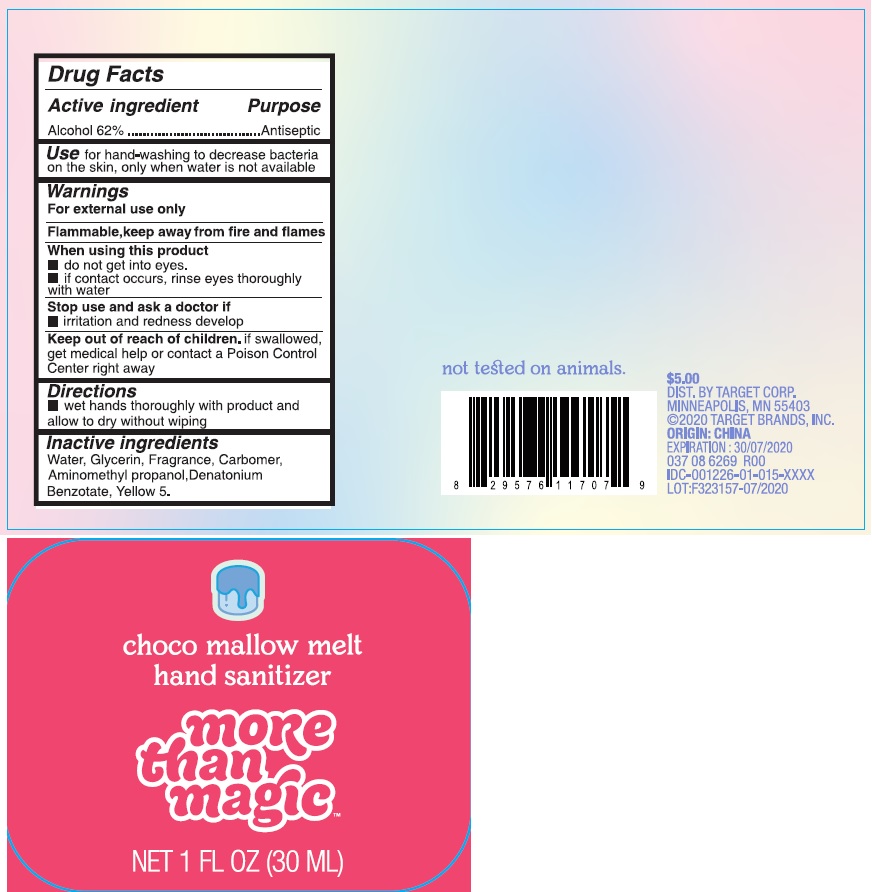 DRUG LABEL: choco mallow melt hand sanitizer
NDC: 11673-079 | Form: GEL
Manufacturer: Target Corporation
Category: otc | Type: HUMAN OTC DRUG LABEL
Date: 20231026

ACTIVE INGREDIENTS: ALCOHOL 0.62 mL/1 mL
INACTIVE INGREDIENTS: WATER; GLYCERIN; CARBOMER HOMOPOLYMER, UNSPECIFIED TYPE; AMINOMETHYLPROPANOL; DENATONIUM BENZOATE; FD&C YELLOW NO. 5

choco mallow melt hand sanitizer

Active ingredient

Alcohol 62%

Purpose

Antiseptic

Use

for hand-washing to decrease bacteria on the skin, only when water is not available.

Warnings

For external use only.

Flammable,keep away from fire and flames

When using this product

- do not get into eyes.
- if contact occurs, rinse eyes thoroughly with water

Stop use and ask a doctor if

irritation and redness develop.

Keep out of reach of children.

If swallowed, get medical help or contact a Poison Control Center right away.

Directions

- wet hands thoroughly with product and allow to dry without wiping.

Inactive ingredients

Water, Glycerin, Fragrance, Carbomer, Aminomethyl propanol,Denatonium Benzotate, Yellow 5.